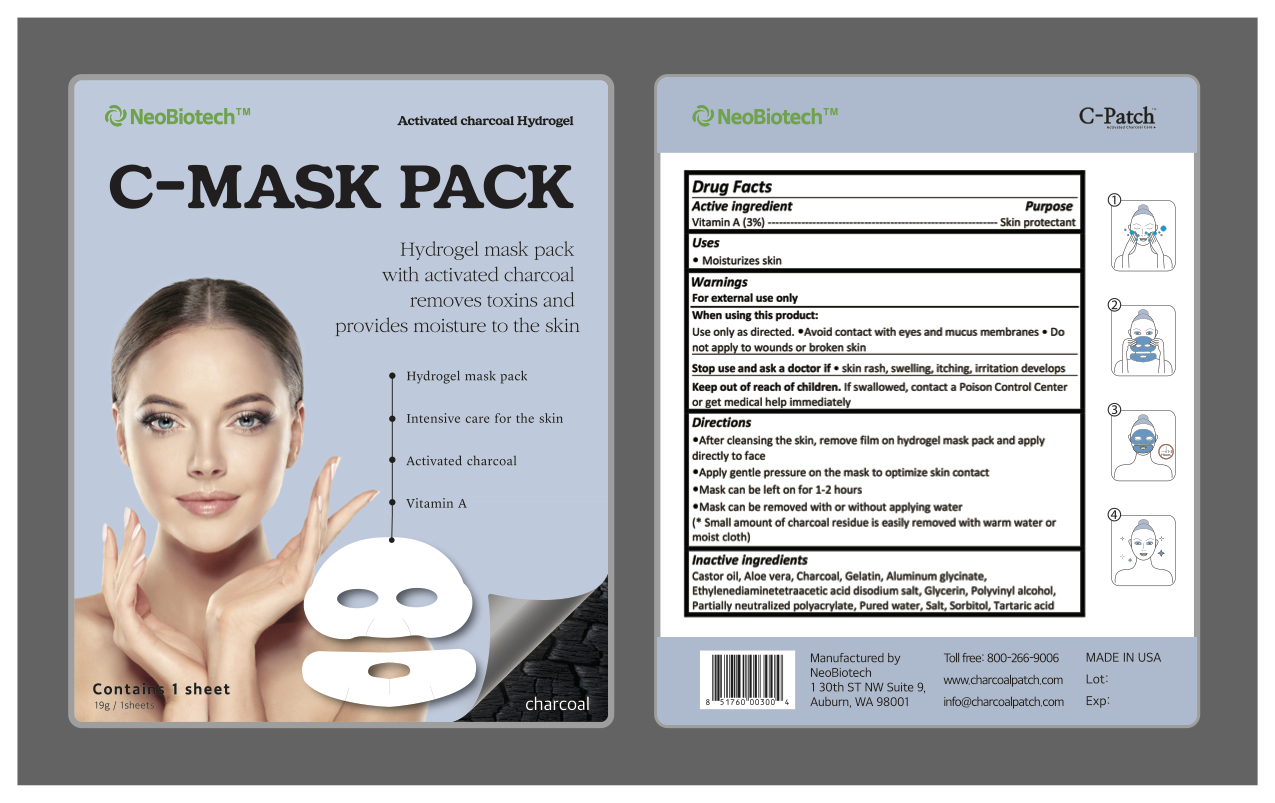 DRUG LABEL: C-Mask Pack
NDC: 70236-105 | Form: PATCH
Manufacturer: NeoBiotech Global Corporation
Category: otc | Type: HUMAN OTC DRUG LABEL
Date: 20180210

ACTIVE INGREDIENTS: VITAMIN A 0.57 g/19 g
INACTIVE INGREDIENTS: CASTOR OIL; POLYVINYL ALCOHOL, UNSPECIFIED; SODIUM CHLORIDE; ALOE VERA WHOLE; ACTIVATED CHARCOAL; GELATIN; DIHYDROXYALUMINUM AMINOACETATE ANHYDROUS; EDETIC ACID; GLYCERIN; WATER; TARTARIC ACID; SORBITOL

C-Mask Pack

Active ingredient

Vitamin A (3%)

Purpose

skin protectant

Uses

moisturizes skin

Warnings

For external use only

When using this product

Use only as directed.

- Do not bandage tightly or use with heating pad

- Avoid contact with eyes and mucus membranes

- Do not appy wounds or broken skin

- Do not apply to large areas of the body

- In case of deep or puncture wounds, animal bites or serious burns, consult a doctor

Stop use and ask a doctor if

- condition worsen

- irritation develops

- symptoms persist for more than 7 days or recurs within 1 day of discontinuation

- do not use for more than 7 days

If pregnant or breast-feeding, ask a health professional before use

Keep out of reach of children. If swallowd, contact a Poison Control Center or get medical help immediately

Directions

- after cleansing the skin, remove film on hydrogel mask pack and apply directly to face.

- apply gentle pressure on the mask to optimize skin contact

- mask can be left on for 1-2 hours

- mask can be removed with or without applying water

(*small amount of charcoal residue is easily removed with warm water or moist cloth)

Inactive ingredients

castor oil, aloe vera, charcoal, gelatin, aluminum glycitnate, ethylenediaminetetraacetic acid disodium salt, glycerin, polyvinyl alcohol, partially neutralized polyacrylate, pured water, salt, sorbitol, tartaric acid

keep out of reach of children. If swallowd, contact a Poison Control Center or get medical help immediately